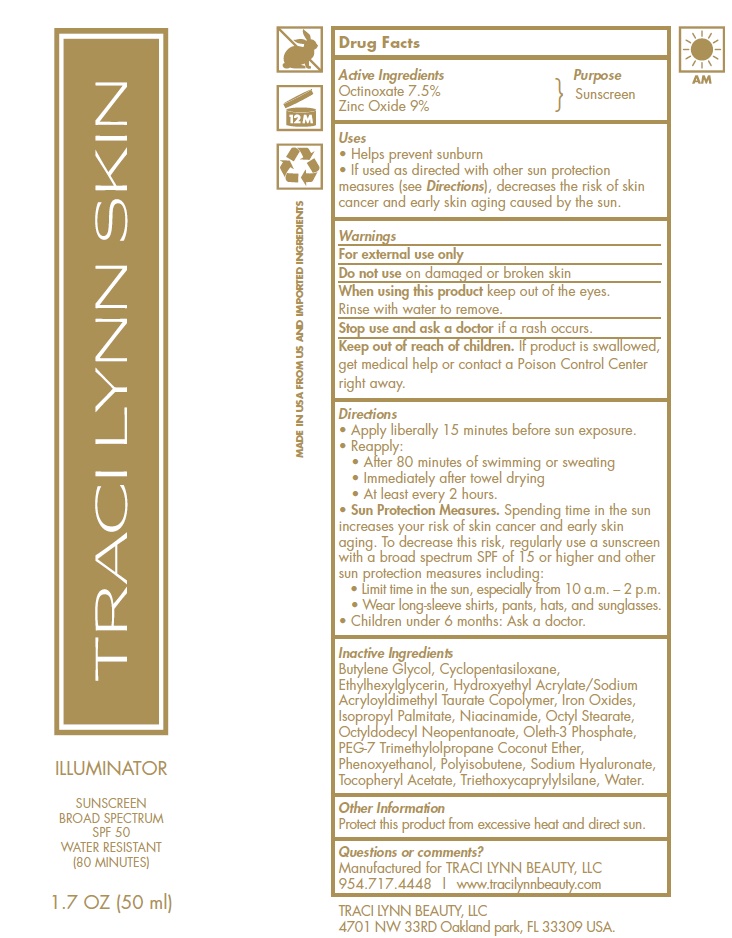 DRUG LABEL: Traci Lynn Skin
NDC: 58443-0296 | Form: LOTION
Manufacturer: Prime Enterprises
Category: otc | Type: HUMAN OTC DRUG LABEL
Date: 20200501

ACTIVE INGREDIENTS: OCTINOXATE 80.475 mg/1 mL; ZINC OXIDE 96.57 mg/1 mL
INACTIVE INGREDIENTS: HYDROXYETHYL ACRYLATE/SODIUM ACRYLOYLDIMETHYL TAURATE COPOLYMER (100000 MPA.S AT 1.5%); HYALURONATE SODIUM; ISOPROPYL PALMITATE; OCTYLDODECYL NEOPENTANOATE; TRIMETHYLOLPROPANE; POLYISOBUTYLENE (1000 MW); NIACINAMIDE; OLETH-3 PHOSPHATE; ETHYLHEXYL STEARATE; BUTYLENE GLYCOL; TRIETHOXYCAPRYLYLSILANE; FERRIC OXIDE RED; FERRIC OXIDE YELLOW; FERROSOFERRIC OXIDE; PHENOXYETHANOL; .ALPHA.-TOCOPHEROL ACETATE; ETHYLHEXYLGLYCERIN; WATER; CYCLOMETHICONE 5

Traci Lynn Skin Illuminator Sunscreen Broad Spectrum SPF 50

Active Ingredients

Octinoxate 7.5%

Zinc Oxide 9%

Purpose

Sunscreen

Uses:

- helps prevent sunburn
- if used as directed with other sun protection measures (see Directions), decreases the risk of skin cancer and early skin aging caused by the sun

Warnings

For external use only

Do not use on damaged or broken skin

When using this product keeo out of the eyes.

Rinse with water to remove.

Stop use and ask a doctor if arash occurs

Kep out of reach of children if product is walloed, get medical help or contact a Poison Control Center right away

Do not use on damaged or broken skin

When using this product keep out of eyes. Rinse with water to remove.

Stop use and ask a doctor if rash occurs.

Keep out of reach of children. If product is swallowed, get medical help or contact a Poison Control Center right away.

Directions

- Apply liberally 15 minutes before sun exposure.
- Reapply:
- After 80 minutes of swimming or sweating
- Immediately after towel drying
- At least every 2 hours.
- Sun Protection Measures. Spending time in the sun increases your risk of skin cancer and early skin aging. To decrease this risk, regularly use a sunscreen with broad spectrum SPF of 15 or higher and other sun protection measures including:
- Limit time in the sun, especially from 10 a.m. – 2 p.m.
- Wear long-sleeve shirts, pants, hats, and sunglasses.
- Children under 6 months: Ask a doctor.

Inactive Ingredients

Butylene Glycol, Cyclopentasiloxane, Ethylhexyl Stearate, Ethylhexylglycerin, Hydroxyethyl Acrylate/Sodium Acryloyldimethyl Taurate Copolymer, Iron Oxides (CI 77491), Iron Oxides (CI 77492), Iron Oxides (CI 77499), Isopropyl Palmitate, Niacinamide, Octyldodecyl Neopentanoate, Oleth-3 Phosphate, PEG-7 Trimethylolpropane Coconut Ether, Phenoxyethanol, Polyisobutene, Sodium Hyaluronate, Tocopheryl Acetate, Triethoxycaprylylsilane, Water

Other information

- Protect this product from excessive heat and direct sun.

Questions or comments?

Mafactured for TRACI LYNN BEAUTY, LLC

954.717.4448 / www.tracilynnbeauty.com